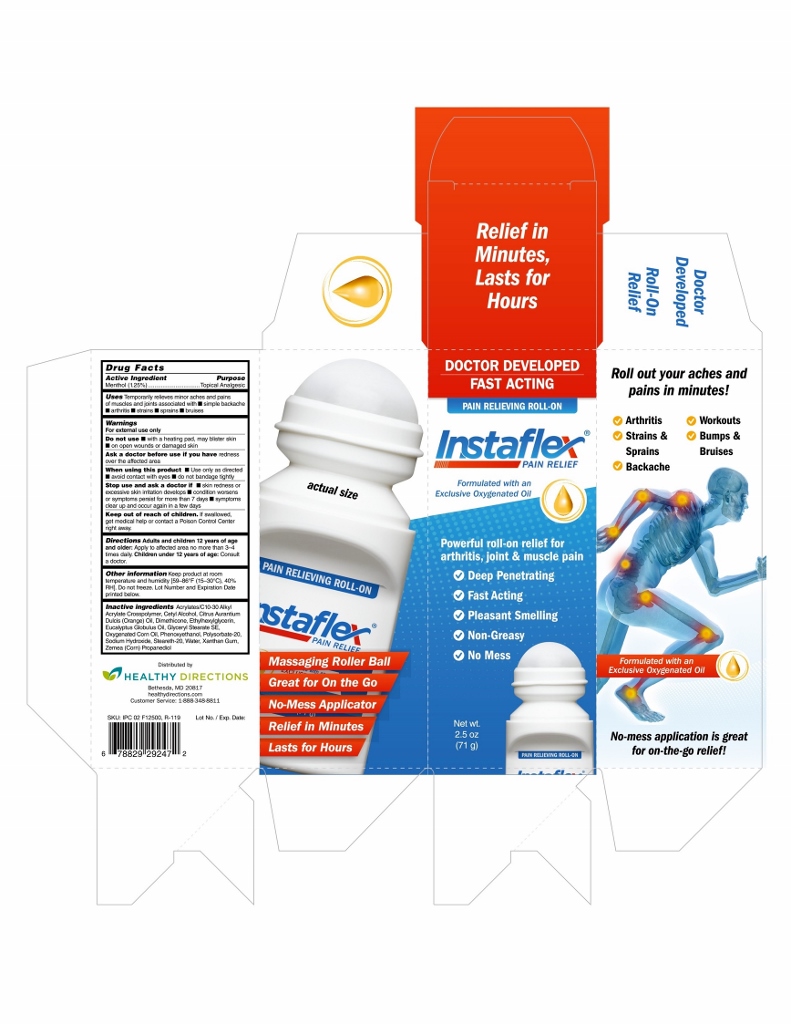 DRUG LABEL: Instaflex Pain Relief Roll-On
NDC: 70015-670 | Form: LIQUID
Manufacturer: Healthy Directions, LLC
Category: otc | Type: HUMAN OTC DRUG LABEL
Date: 20191021

ACTIVE INGREDIENTS: MENTHOL 12.5 mg/1 g
INACTIVE INGREDIENTS: CORN OIL; PHENOXYETHANOL; ETHYLHEXYLGLYCERIN; POLYSORBATE 20; SODIUM HYDROXIDE; STEARETH-20; WATER; ORANGE OIL; EUCALYPTUS OIL; GLYCERYL STEARATE SE; XANTHAN GUM; PROPANEDIOL; CARBOMER INTERPOLYMER TYPE A (ALLYL SUCROSE CROSSLINKED); CETYL ALCOHOL; DIMETHICONE

InstaFlex Pain Relieving Roll-On

Active Ingredient

Menthol (1.25%)

Purpose

Menthol (1.25%)....................Topical Analgesic

Uses

Temporarily relieves minor aches and pains of muscles and joints associated with

- arthritis
- strains
- sprains
- bruises

Warnings

For external use only

Do not use

- with a heating pad, may blister skin
- on open wounds or damaged skin

Ask a doctor before use if you have redness over the affected area

When using this product

- Use only as directed
- avoid contact with eyes
- do not bandage tightly

Stop use and ask a doctor if

- skin redness or excessive skin irritation develops
- condition worsens or symptoms persist for more than 7 days
- symptoms clear up and occur again in a few days

Keep out of reach of children. If swallowed, get medical help or contact a Poison Control Center right away.

Directions

Adult and children 12 years of age and older: Apply to affected area no more than 3-4 times daily.

Children under 12 years of age: Consult a doctor.

Other information

Keep product at room termperature and humidity [59-86°F (15-30°C), 40% RH]. Do not freeze. Lot Number and Expiration Date printed below.

Inactive ingredients

Acrylates/C10-30 Alkyl Acrylate Crosspolymer, Cetyl Alcohol, Citrus Aurantium Dulcis (Orange) Oil, Dimethicone, Ethylhexylglycerin, Eucalyptus Globulus Oil, Clyceryl Stearate SE, Oxygenated Corn Oil, Phenoxyethanol, Polysorbate-20, Sodium Hydroxide, Steareth-20, Water, Xanthan Gum, Zemea (Corn) Propanediol

PACKAGE LABEL

DOCTOR DEVELOPED

FAST ACTING

PAIN RELIEVING ROLL-ON

Instaflex

PAIN RELIEF

Formualted with an Exclusive Oxygenated Oil

Powerful roll-on relief for arthritis, joint & muscle pain

- Deep Penetrating
- Fast Acting
- Pleasant Smelling
- Non-Greasy
- No Mess

Net wt. 2.5 oz (71 g)